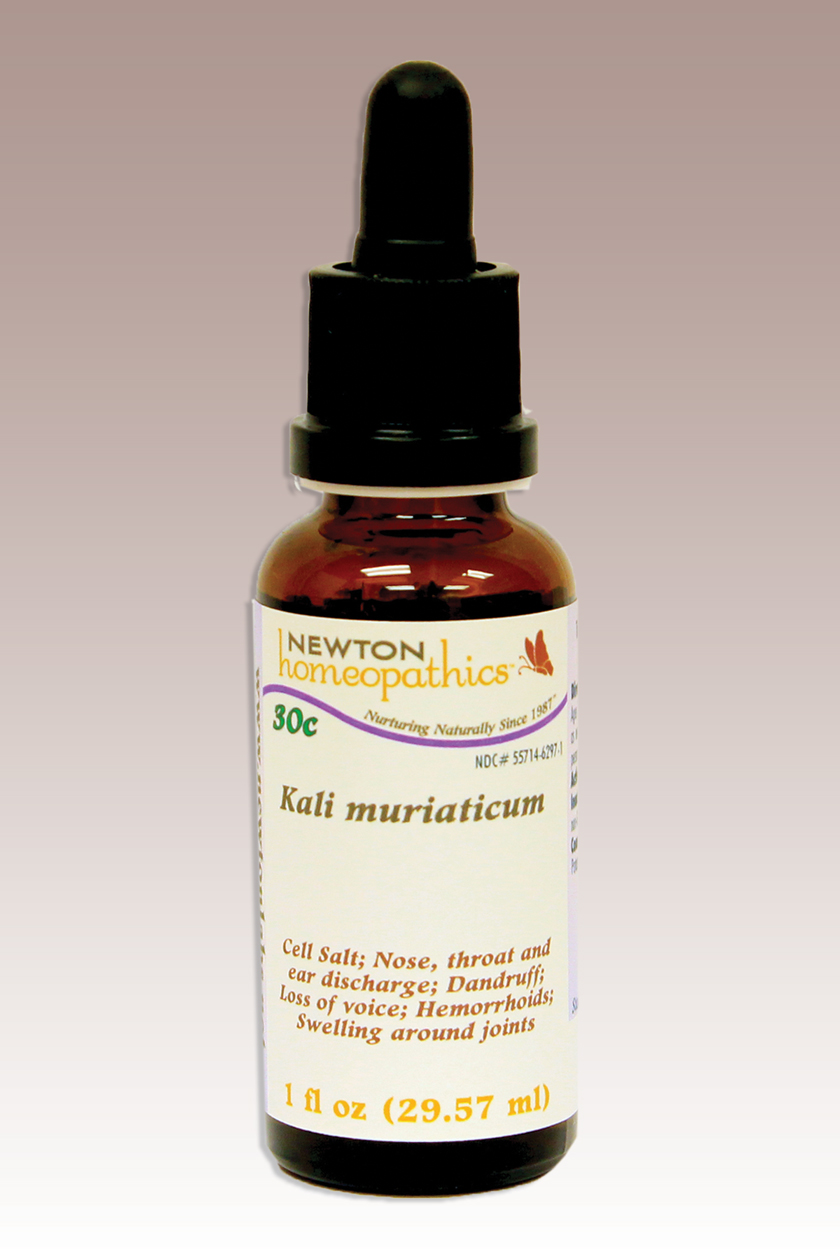 DRUG LABEL: Kali muriaticum 
NDC: 55714-6297 | Form: LIQUID
Manufacturer: Newton Laboratories, Inc.
Category: homeopathic | Type: HUMAN OTC DRUG LABEL
Date: 20110901

ACTIVE INGREDIENTS: Potassium Chloride 15 [hp_X]/1 mL
INACTIVE INGREDIENTS: Alcohol; Water

Kali muriaticum

INDICATIONS & USAGE SECTION

Cell Salt; Nose, throat & ear discharge; Dandruff; Loss of voice; Hemorrhoids, Swelling around joints.

DOSAGE & ADMINISTRATION SECTION

Directions: Ages 12 and up, take 6 drops by mouth (ages 0 to 11, give 3 drops) as needed or as directed by a health professional. Sensitive persons begin with 1 drop and gradually increase to full dose.

OTC - ACTIVE INGREDIENT SECTION

Kali muriaticum 15x, 10x, 200c, 30c.

OTC - PURPOSE SECTION

Cell Salt; Nose, throat & ear discharge; Dandruff; Loss of voice; Hemorrhoids, Swelling around joints.

INACTIVE INGREDIENT SECTION

Inactive Ingredients: USP Purified water; USP Gluten-free, non-GMO, organic cane alcohol 20%.

QUESTIONS SECTION

www.newtonlabs.net Newton Laboratories, Inc. FDA Est # 1051203 - Conyers, GA 30012
Questions? 1.800.448.7256

WARNINGS SECTION

WARNINGS: Keep out of reach of children. Do not use if tamper-evident seal is broken or missing. If symptoms worsen or persist for more than a few days, consult a doctor. If pregnant or breast-feeding, ask a doctor before use.

OTC - PREGNANCY OR BREAST FEEDING SECTION

If pregnant or breast-feeding, ask a doctor before use.

OTC - KEEP OUT OF REACH OF CHILDREN SECTION

Keep out of reach of children.